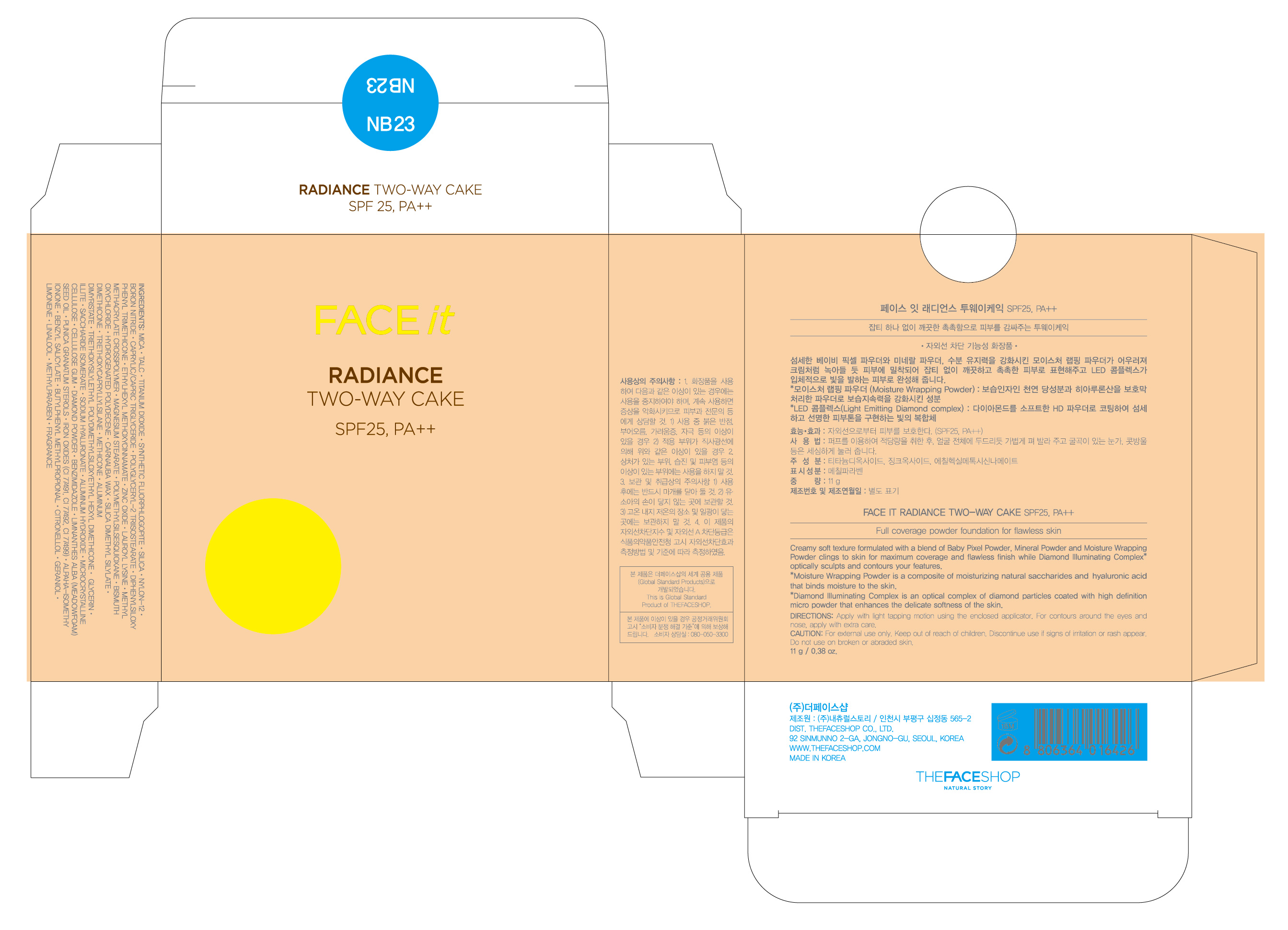 DRUG LABEL: FACE IT Radiance Two Way Cake NB23
NDC: 51523-113 | Form: POWDER
Manufacturer: THEFACESHOP CO., LTD
Category: otc | Type: HUMAN OTC DRUG LABEL
Date: 20110901

ACTIVE INGREDIENTS: TITANIUM DIOXIDE 12.8784 g/100 g; OCTINOXATE 2 g/100 g; ZINC OXIDE 1.4775 g/100 g
INACTIVE INGREDIENTS: MICA; DIMETHICONE; TRIETHOXYCAPRYLYLSILANE; ALUMINUM DIMYRISTATE; SILICON DIOXIDE; ALUMINUM HYDROXIDE; CELLULOSE, MICROCRYSTALLINE; CARBOXYMETHYLCELLULOSE SODIUM; BORON NITRIDE; DIISOPROPYL ADIPATE; GLYCERIN; LAUROYL LYSINE; MAGNESIUM STEARATE; BISMUTH OXYCHLORIDE; FERRIC OXIDE RED; CARNAUBA WAX; METHYLPARABEN; FERRIC OXIDE YELLOW; BENZIMIDAZOLE; MEADOWFOAM SEED OIL; SACCHARIDE ISOMERATE; HYALURONATE SODIUM; GLYCERIN

FACE IT Radiance Two Way Cake NB23

ACTIVE INGREDIENT

TITANIUM DIOXIDE (12.8784%)
OCTINOXATE (2%)
ZINC OXIDE (1.4775%)

WARNINGS AND PRECAUTIONS

For external use only

Keep out of reach of children. Is swallowed, get medical help or contact a Poison Control Center right away.

WHEN USING

Keep out of eyes. Rinse with water to remove.

Stop use if a rash or irritation develops and lasts.

PACKAGE LABEL

FACE IT Radiance Two Way Cake NB2